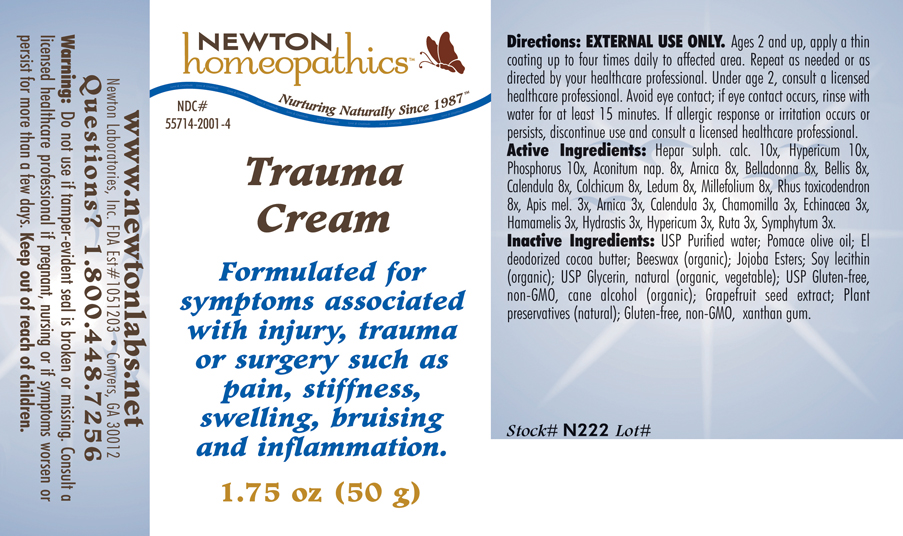 DRUG LABEL: Trauma Cream 
NDC: 55714-2001 | Form: CREAM
Manufacturer: Newton Laboratories, Inc.
Category: homeopathic | Type: HUMAN OTC DRUG LABEL
Date: 20130801

ACTIVE INGREDIENTS: Calcium Sulfide 10 [hp_X]/1 g; Hypericum Perforatum 10 [hp_X]/1 g; Phosphorus 10 [hp_X]/1 g; Aconitum Napellus 8 [hp_X]/1 g; Arnica Montana 8 [hp_X]/1 g; Atropa Belladonna 8 [hp_X]/1 g; Bellis Perennis 8 [hp_X]/1 g; Calendula Officinalis Flowering Top 8 [hp_X]/1 g; Colchicum Autumnale Bulb 8 [hp_X]/1 g; Ledum Palustre Twig 8 [hp_X]/1 g; Achillea Millefolium 8 [hp_X]/1 g; Toxicodendron Pubescens Leaf 8 [hp_X]/1 g; Apis Mellifera 3 [hp_X]/1 g; Matricaria Recutita 3 [hp_X]/1 g; Echinacea, Unspecified 3 [hp_X]/1 g; Hamamelis Virginiana Root Bark/stem Bark 3 [hp_X]/1 g; Goldenseal 3 [hp_X]/1 g; Ruta Graveolens Flowering Top 3 [hp_X]/1 g; Comfrey Root 3 [hp_X]/1 g
INACTIVE INGREDIENTS: Water; Olive Oil; Cocoa Butter; Royal Jelly; Jojoba Oil; Lecithin, Soybean; Glycerin; Alcohol; Citrus Paradisi Seed; Lonicera Japonica Flower; Xanthan Gum

Trauma Cream

INDICATIONS & USAGE SECTION

Trauma Cream: Formulated for symptoms associated with injury, trauma or surgery such as pain, stiffness, swelling, bruising and inflammation.

DOSAGE & ADMINISTRATION SECTION

Directions: EXTERNAL USE ONLY. Ages 2 and up, apply a thin coating up to four times daily to affected area. Repeat as needed or as directed by your healthcare professional. Under age 2, consult a licensed healthcare professional. Avoid eye contact; if eye contact occurs, rinse with water for at least 15 minutes. If allergic response or irritation occurs or persists, discontinue use and consult a licensed healthcare professional.

OTC - ACTIVE INGREDIENT SECTION

Hepar sulph. calc. 10x, Hypericum 10x, Phosphorus 10x, Aconitum nap. 8x, Arnica 8x, Belladonna 8x, Bellis 8x, Calendula 8x, Colchicum 8x, Ledum 8x, Millefolium 8x, Rhus toxicodendron 8x, Apis mel. 3x, Arnica 3x, Calendula 3x, Chamomilla 3x, Echinacea 3x, Hamamelis 3x, Hydrastis 3x, Hypericum 3x, Ruta 3x, Symphytum 3x.

OTC - PURPOSE SECTION

Formulated for symptoms associated with injury, trauma or surgery such as pain, stiffness, swelling, bruising and inflammation.

INACTIVE INGREDIENT SECTION

Inactive Ingredients: USP Purified Water, Pomace Olive Oil, El Deodorized Cocoa Butter, Beeswax (organic), Jojoba Esters, Soy Lecithin (organic), USP Glycerin, natural (organic, vegetable), USP Gluten-free, non-GMO Cane Alcohol (organic), Grapefruit Seed Extract, Plant preservatives (natural), Gluten-free, non-GMO Xanthan Gum.

OTC - QUESTIONS SECTION

www.newtonlabs.net Newton Laboratories, Inc. FDA Est # 1051203 - Conyers, GA 30012 Questions? 1.800.448.7256

WARNINGS SECTION

Warning: Do not use if tamper - evident seal is broken or missing. Consult a licensed healthcare professional if pregnant, nursing or if symptoms worsen or persist for more than a few days. Keep out of reach of children.

OTC - PREGNANCY OR BREAST FEEDING SECTION

Consult a licensed healthcare professional if pregnant, nursing or if symptoms worsen or persist for more than a few days.

OTC - KEEP OUT OF REACH OF CHILDREN SECTION

Keep out of reach of children